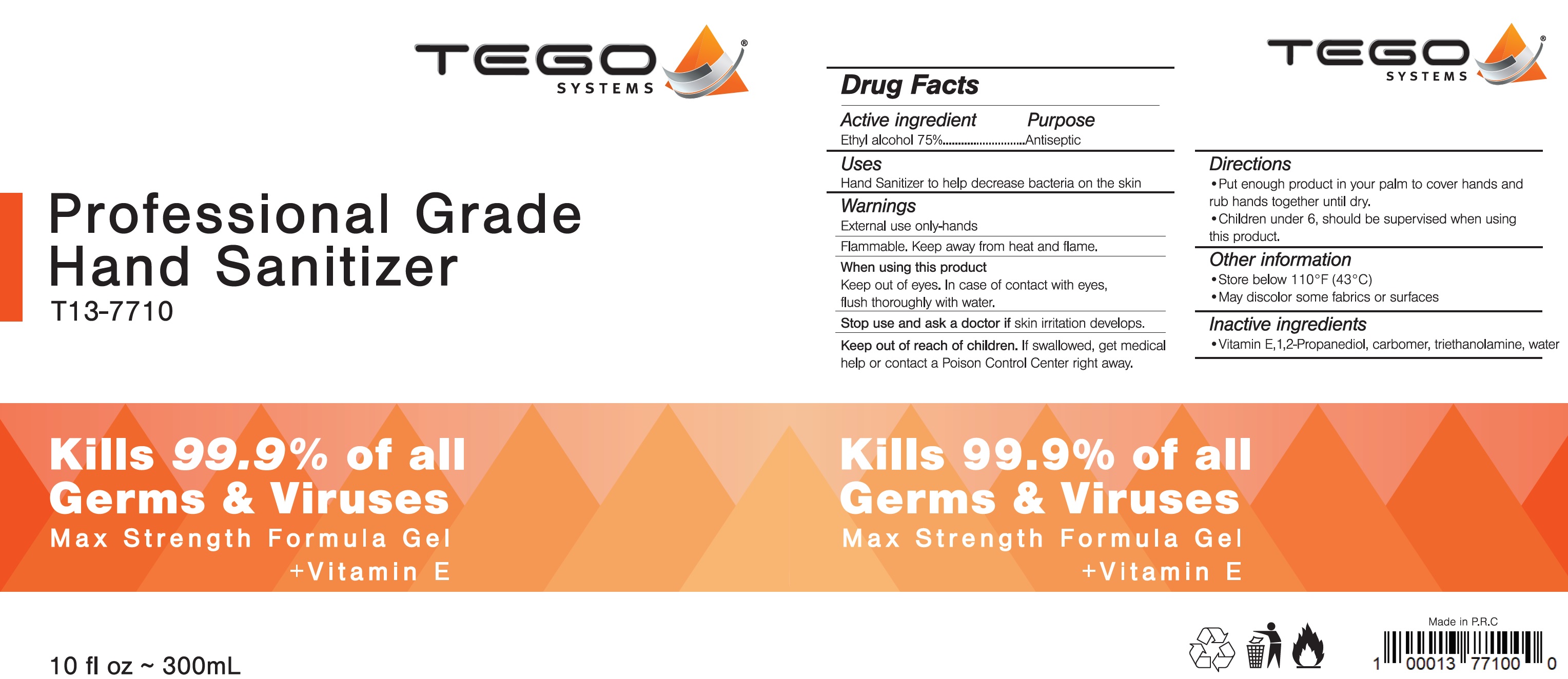 DRUG LABEL: Tego Systems Professional Grade Hand Sanitizer
NDC: 81497-700 | Form: GEL
Manufacturer: Tego systems Corp
Category: otc | Type: HUMAN OTC DRUG LABEL
Date: 20210202

ACTIVE INGREDIENTS: ALCOHOL 75 mL/100 mL
INACTIVE INGREDIENTS: .ALPHA.-TOCOPHEROL; PROPYLENE GLYCOL; CARBOMER HOMOPOLYMER, UNSPECIFIED TYPE; TROLAMINE; WATER

Tego Systems Professional Grade Hand Sanitizer

Active ingredient

Ethyl alcohol 75%

Purpose

Antiseptic

Uses

Hand Sanitizer to help decrease bacteria on the skin

Warnings

External use only-hands

Flammable. Keep away from heat or flame.

When using this product

Keep out of eyes. In case of contact with eyes, flush thoroughly with water.

Stop use and ask a doctor if

skin irritation develops.

Keep out of reach of children.

If swallowed, get medical help or contact a Poison control Center right away.

Directions

- Put enough product in your palm to cover hands and rub hands together until dry.
- Children under 6, should be supervised when using this product.

Other information

- Store below 110°F (43°C)
- May discolor some fabrics or surfaces

Inactive ingredients

- Vitamin E, 1,2-Propanediol, carbomer, triethanolamine, water